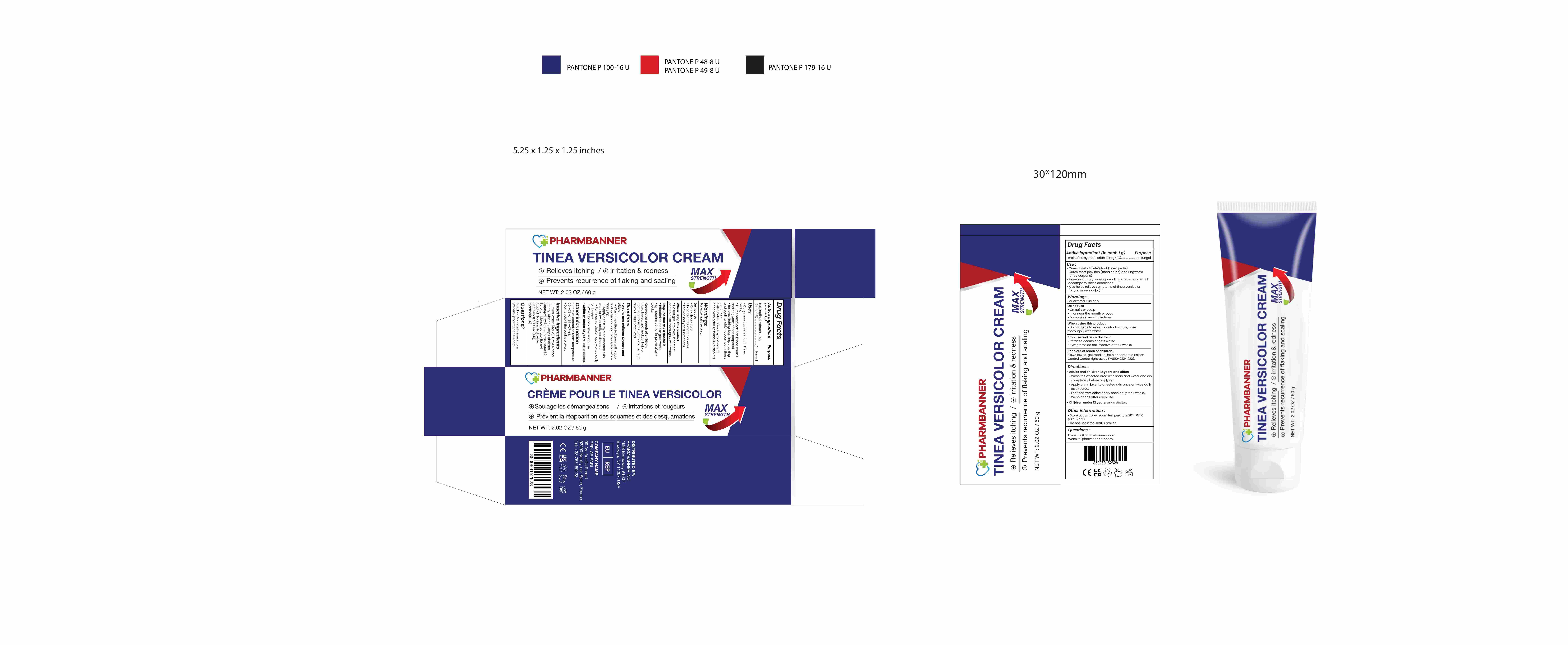 DRUG LABEL: PHARMBANNER TINEA VERSICOLOR Cream
NDC: 83818-024 | Form: CREAM
Manufacturer: Shenzhen Xinxin Yunhai Technology Co., Ltd.
Category: otc | Type: HUMAN OTC DRUG LABEL
Date: 20260212

ACTIVE INGREDIENTS: TERBINAFINE HYDROCHLORIDE 1 g/100 g
INACTIVE INGREDIENTS: SORBITAN MONOSTEARATE; ISOPROPYL MYRISTATE; UREA; CETYL PALMITATE; WATER; STEARYL ALCOHOL; CETYL ALCOHOL; POLYSORBATE 60; SODIUM HYDROXIDE; PANTHENOL; MENTHOL; BENZYL ALCOHOL

83818-024 Update Manufacturer

Active Ingredient

Terbinafine hydrochloride 1%

Purpose

Antifungal

Use

• Cures most athlete’s foot (tinea pedis)
• Cures most jock itch (tinea cruris) and ringworm (tinea corporis)
• Relieves itching, burning, cracking and scaling which accompany these conditions
• Also helps relieve symptoms of tinea versicolor (pityriasis versicolor)

Warnings

For external use only.

Do not use

• On nails or scalp
• In or near the mouth or eyes
• For vaginal yeast infections

When Using

• Do not get into eyes. If contact occurs, rinse thoroughly with water.

Stop Use

• Irritation occurs or gets worse
• Symptoms do not improve after 4 weeks

Ask Doctor

• Irritation occurs or gets worse
• Symptoms do not improve after 4 weeks

Keep Out Of Reach Of Children

If swallowed, get medical help or contact a Poison Control Center right away (1-800-222-1222).

Directions

• Adults and children 12 years and older:
- Wash the affected area with soap and water and dry completely before applying.
- Apply a thin layer to affected skin once or twice daily as directed.
- For tinea versicolor: apply once daily for 2 weeks.
- Wash hands after each use.
• Children under 12 years: ask a doctor.

Other information

• Store at controlled room temperature 20°–25 °C (68°–77 °F).
• Do not use if the seal is broken.

Inactive ingredients

Purified Water (Aqua), Cetyl Alcohol, Stearyl Alcohol, Cetyl Palmitate, Isopropyl Myristate, Polysorbate 60, Sorbitan Monostearate, Benzyl Alcohol, Sodium Hydroxide, Panthenol(1%), Urea(4%), Menthol(0.5%)

Questions

Email: cs@pharmbanners.com
Website: pharmbanners.com